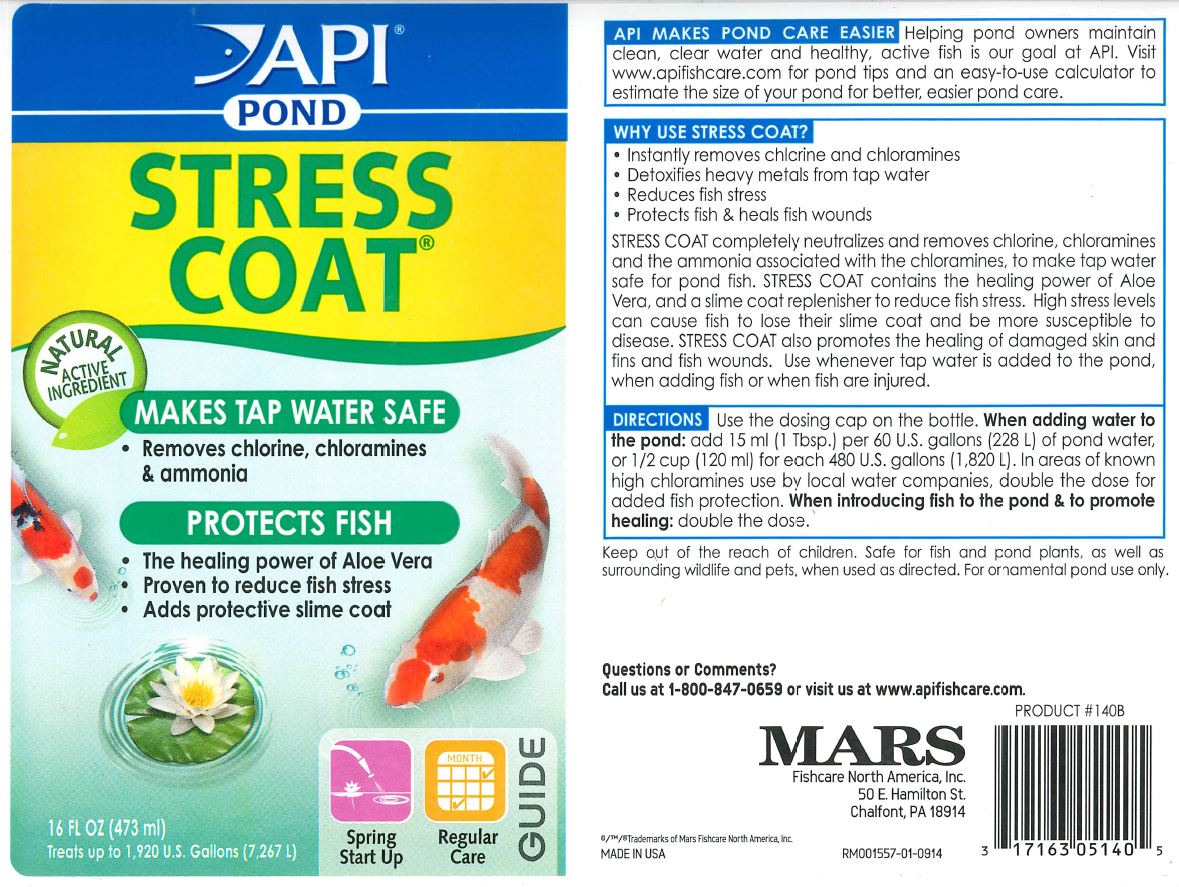 DRUG LABEL: API Pond Stress Coat
NDC: 17163-140 | Form: LIQUID
Manufacturer: MARS FISHCARE NORTH AMERICA, INC
Category: animal | Type: OTC ANIMAL DRUG LABEL
Date: 20191219

ACTIVE INGREDIENTS: ALOE VERA LEAF 0.05 g/100 mL

Drug Facts

DESCRIPTION

API MAKES POND CARE EASIER

Helping pond owners maintain clean, clear water and healthy, active fish is our goal at API. Visit www.apifishcare.com for pond tips and an easy-to-use calculator to estimate the size of your pond for better, easier pond care.

INDICATIONS AND USAGE

WHY USE STREE COAT?

Instantly removes chlorine and chloramines

Detoxifies heavy metals from tap water

Reduces fish stress

Protects fish and heals fish wounds

STRESS COAT completely neutralizes and removes chlorine, chloramines and the ammonia associated with the chloramines, to make tap water safe for pond fish.

STRESSCOAT contains the healing power of Aloe Vera, and a slime replenisher to reduce fish stress. High stress levels can cause fish to lose their slime coat and be more susceptible to disease.

STRESS COAT also promotes the healing of damaged skin and fins and wounds. Use whenever tap water is added to the pond, when adding fish or when fish are injured.

DIRECTIONS

Use the dosage cap on the bottle.

When adding water to the pond: add 15 ml (1 Tbsp.) per 60 U.S. gallons (228 L) of pond water, or 1/2 cup (120 ml) for each 480 U.S. gallons (1,820 L).

In areas of known high choramines use by local water companies, double the dose for added fish protection.

When introducing fish to the pond and to promote healing: double the dose.

WARNINGS AND PRECAUTIONS

Keep out of the reach of children.

Safe for fish and pond plants, as well as surrounding wildlife and pests, when used as directed.

For ornamental pond use only.

Questions or Comments?

Call us at 1-800-847-0659 or visit us at www.apifischcare.com

PACKAGE LABEL

API

POND

STRESS

COAT

NATURAL ACTIVE INGREDIENT

MAKES TAP WATER SAFE

Removes chlorine, chloramines and ammonia

PROTECTS FISH

The healing power of Aloe Vera

Proven to reduce fish stress

Adds protective slime coat

16 FL OZ (473 ml)

Treats up to 1,920 U.S. Gallons (7,267 L)

Spring Start Up

Regular Care

GUIDE